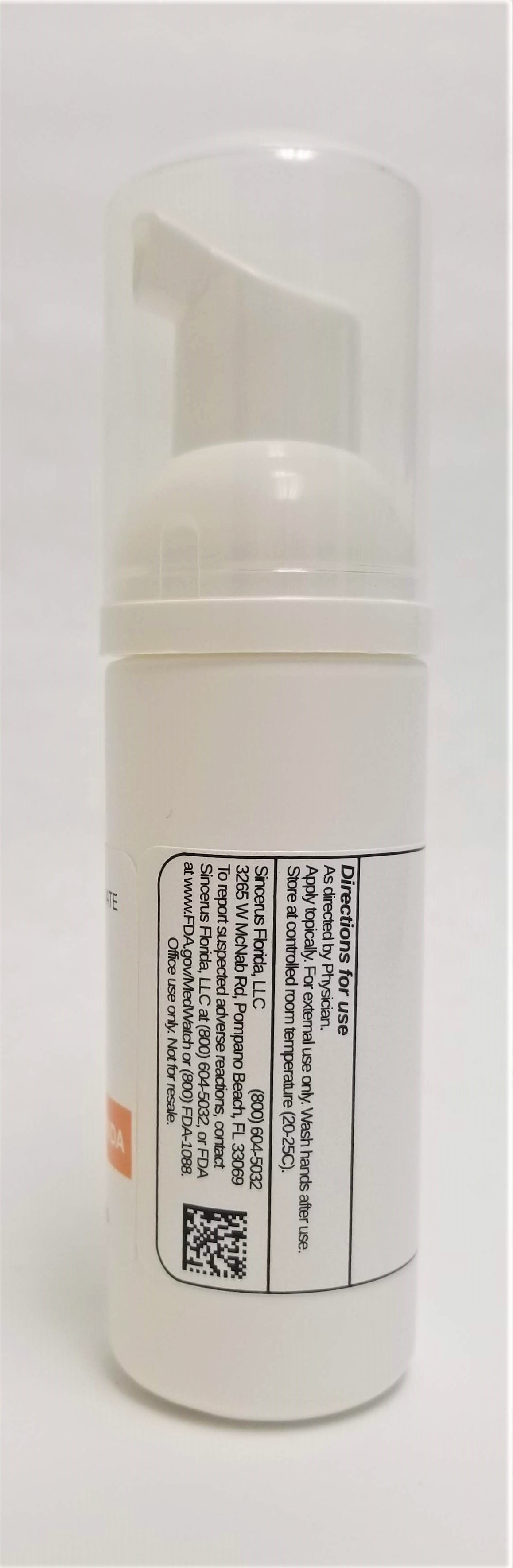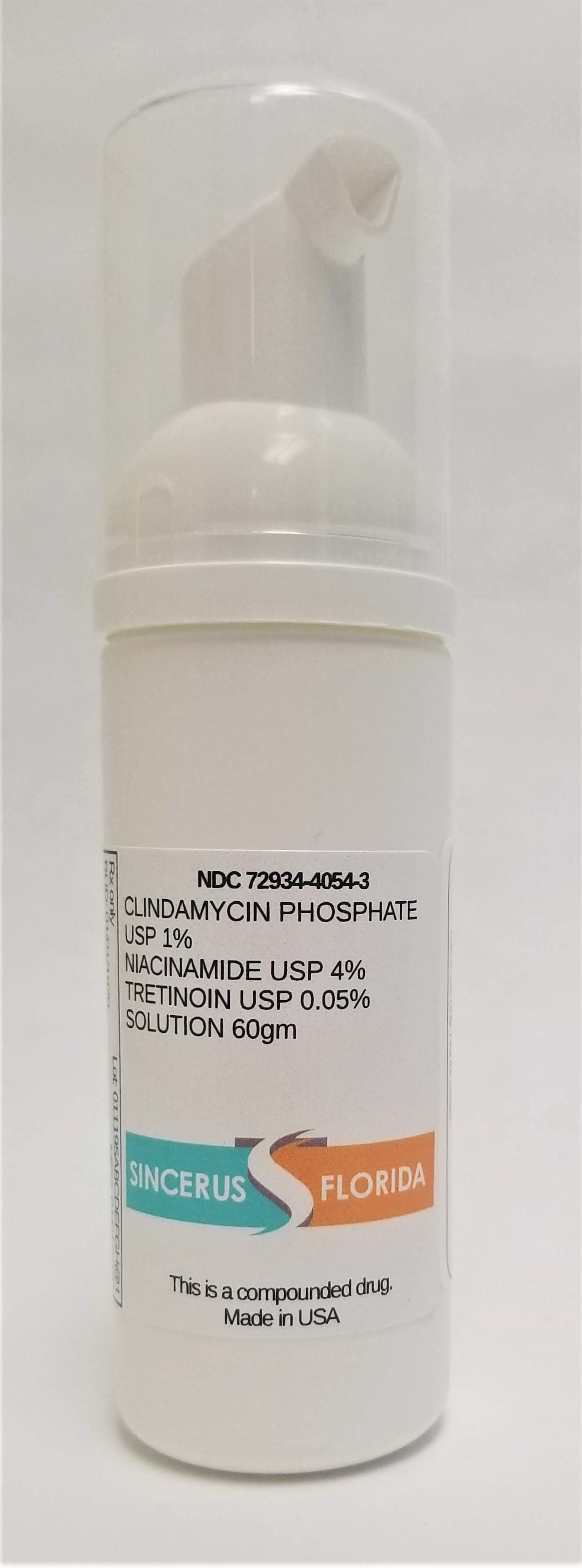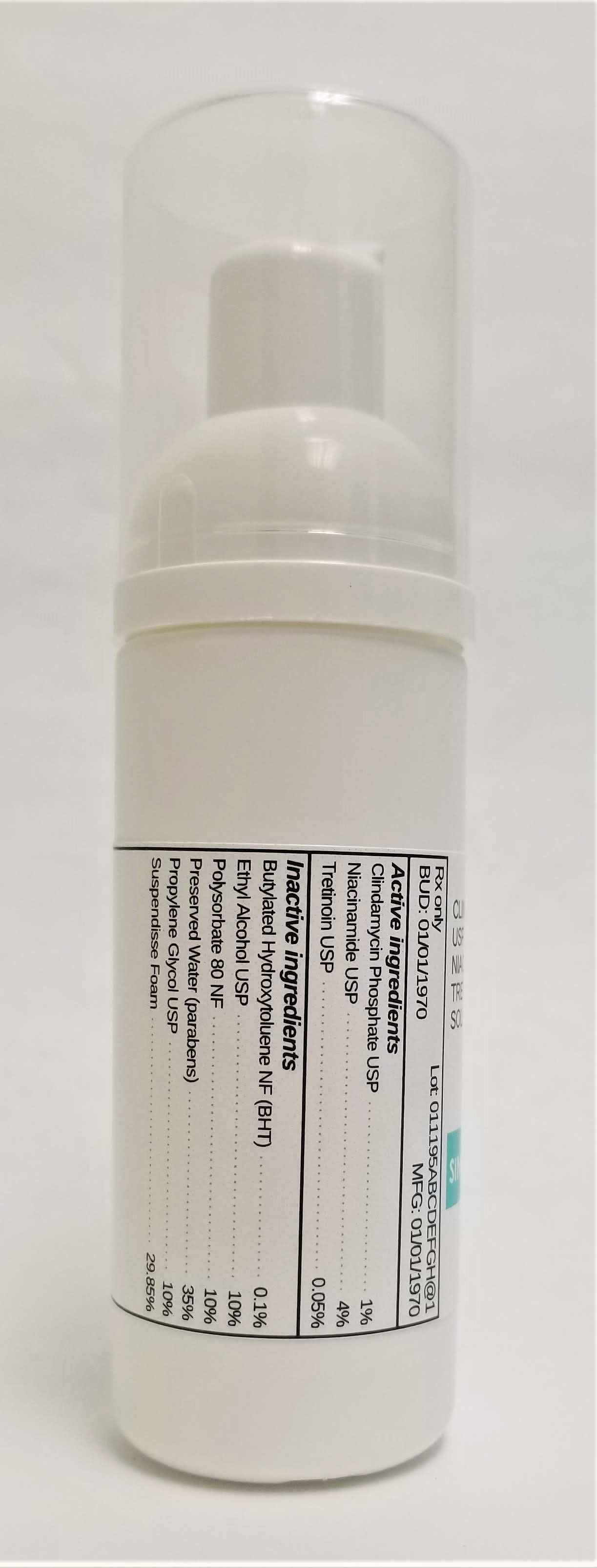 DRUG LABEL: CLINDAMYCIN 1% / NIACINAMIDE 4% / TRETINOIN 0.05%
NDC: 72934-4054 | Form: SOLUTION
Manufacturer: Sincerus Florida, LLC
Category: prescription | Type: HUMAN PRESCRIPTION DRUG LABEL
Date: 20190506

ACTIVE INGREDIENTS: CLINDAMYCIN PHOSPHATE 1 g/100 g; NIACINAMIDE 4 g/100 g; TRETINOIN 0.05 g/100 g

CLINDAMYCIN 1% / NIACINAMIDE 4% / TRETINOIN 0.05%